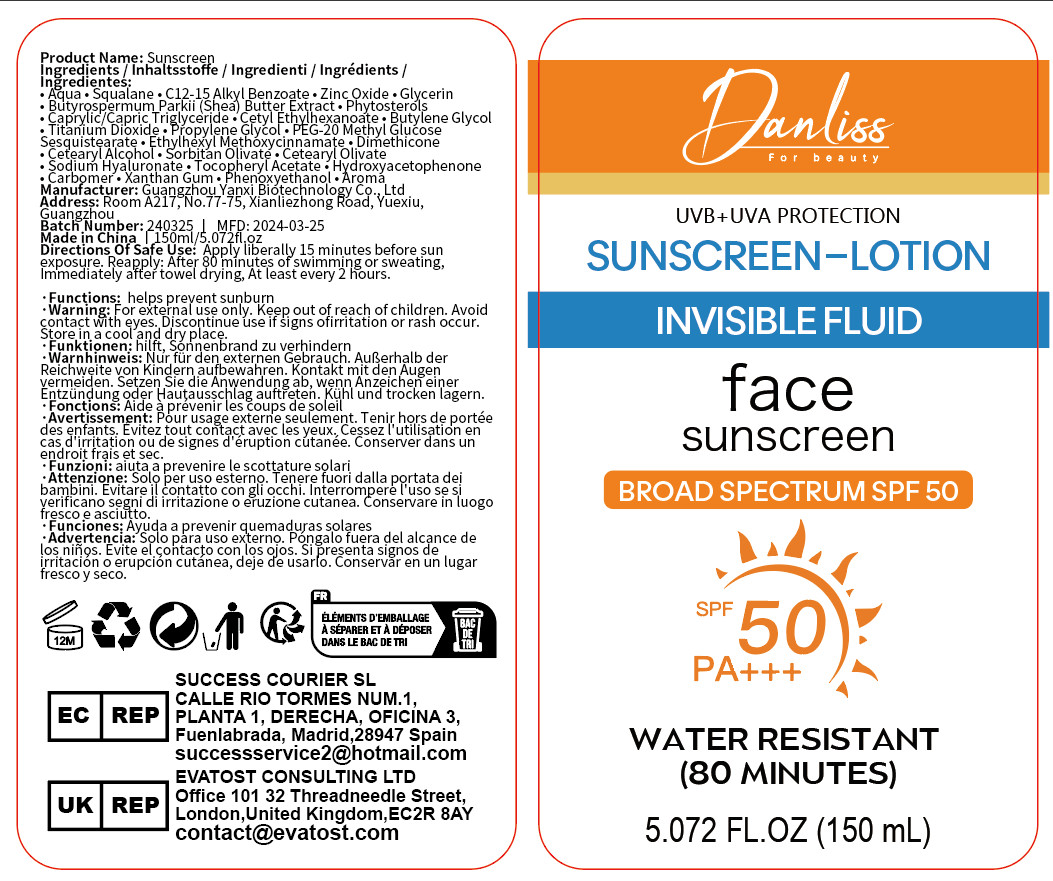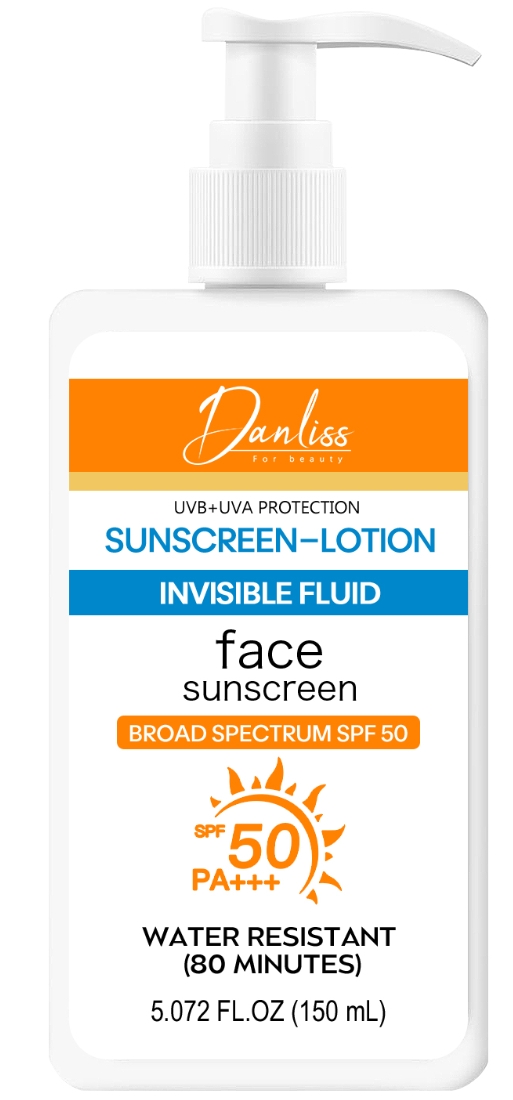 DRUG LABEL: Sunscreen Moisturizer
NDC: 84025-142 | Form: CREAM
Manufacturer: Guangzhou Yanxi Biotechnology Co., Ltd
Category: otc | Type: HUMAN OTC DRUG LABEL
Date: 20240326

ACTIVE INGREDIENTS: ZINC OXIDE 135 mg/1 mL; SQUALANE 100 mg/1 mL
INACTIVE INGREDIENTS: WATER

WARNINGS

Keep ouf of Children

DOSAGE AND ADMINISTRATION

Apply liberally 15 minutes before sun exposure. Reapply: After 80 minutes of swimming or sweating,
Immediately after towel drying, At least every 2 hours.

INDICATIONS AND USAGE

Apply liberally 15 minutes before sun exposure. Reapply: After 80 minutes of swimming or sweating,
Immediately after towel drying, At least every 2 hours.

INACTIVE INGREDIENT

water